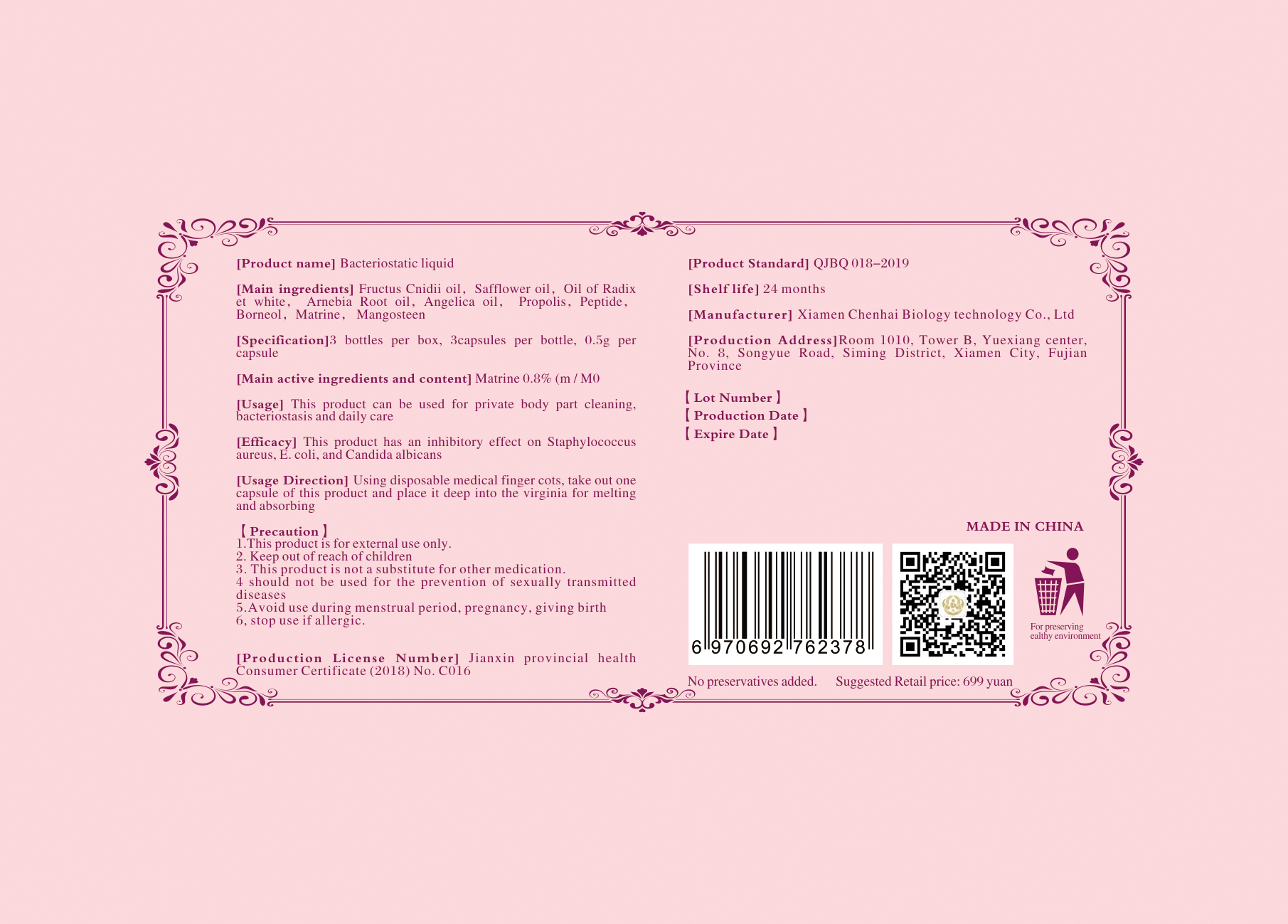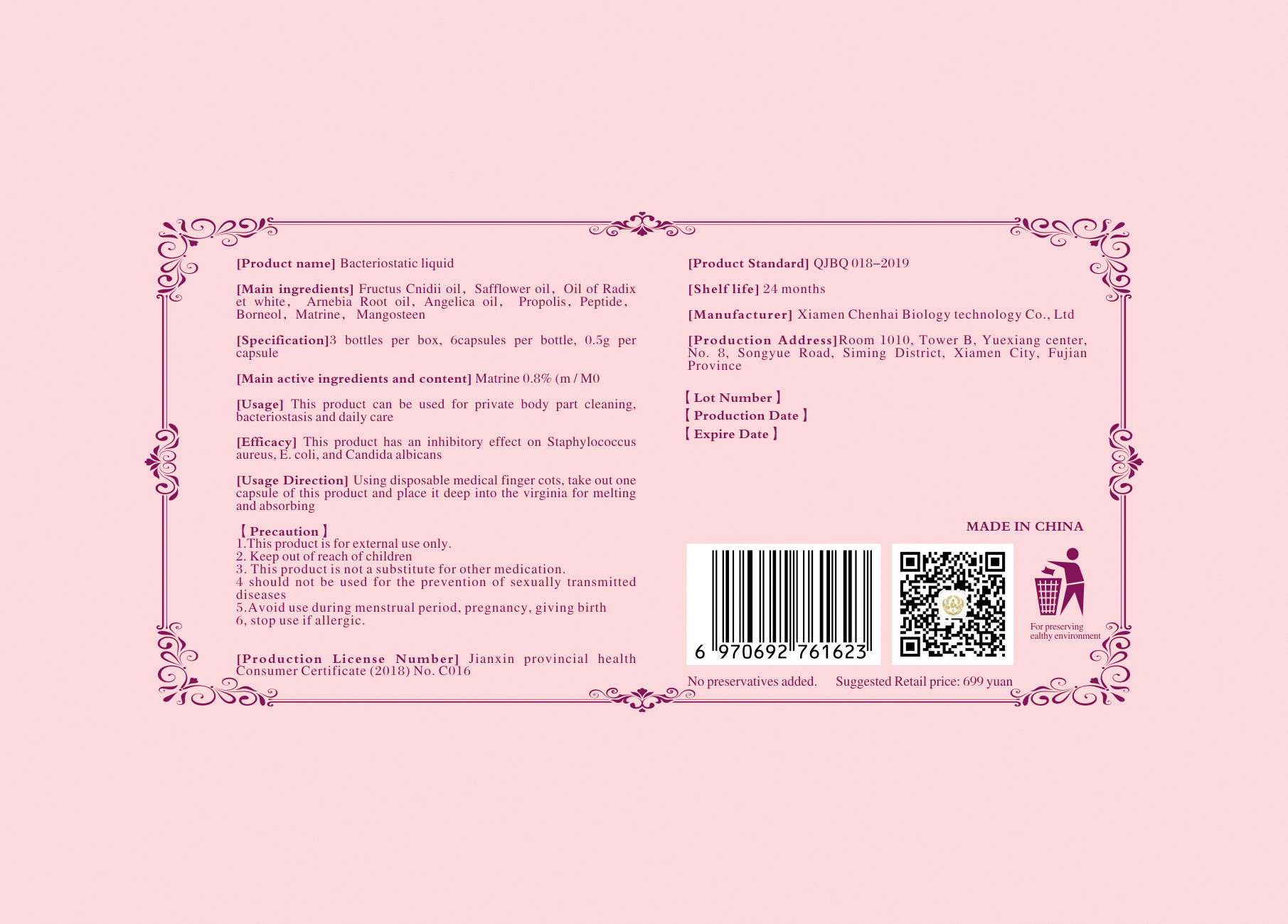 DRUG LABEL: antiseptic solution
NDC: 74756-001 | Form: LIQUID
Manufacturer: Xiamen chenhai biotechnology co.LTD
Category: otc | Type: HUMAN OTC DRUG LABEL
Date: 20220704

ACTIVE INGREDIENTS: MATRINE 0.8 g/100 g
INACTIVE INGREDIENTS: ANGELICA SEED OIL; PROPOLIS WAX; SAFFLOWER OIL; BORNEOL

Bacteriostatic liquid

active ingredients

Matrine 0.8%(m/M0)

Usage

This product can be used for private body part cleaning, bacteriostasis and daily care.

Directions

Using disposable medical finger cots,take out one capsule of this product and place it deep into the virginia for melting and absorbing.

Other information

1.This product is for external use only.

2.Keep out of reach of children.

3.This product is not a substitute for other medication.

4 should not be used for the prevention of sexually transmitted diseases.

5.Avoid use during menstrual period, pregnancy, giving birth.

6,stop use if allergic.

Inactive Ingredients

Fructus Cnidii oil,safflower oil,Oil of Radix et white,Arnebia Root oil,Angelica oil,Propolis,Peptide,Borneol,Mangosteen.